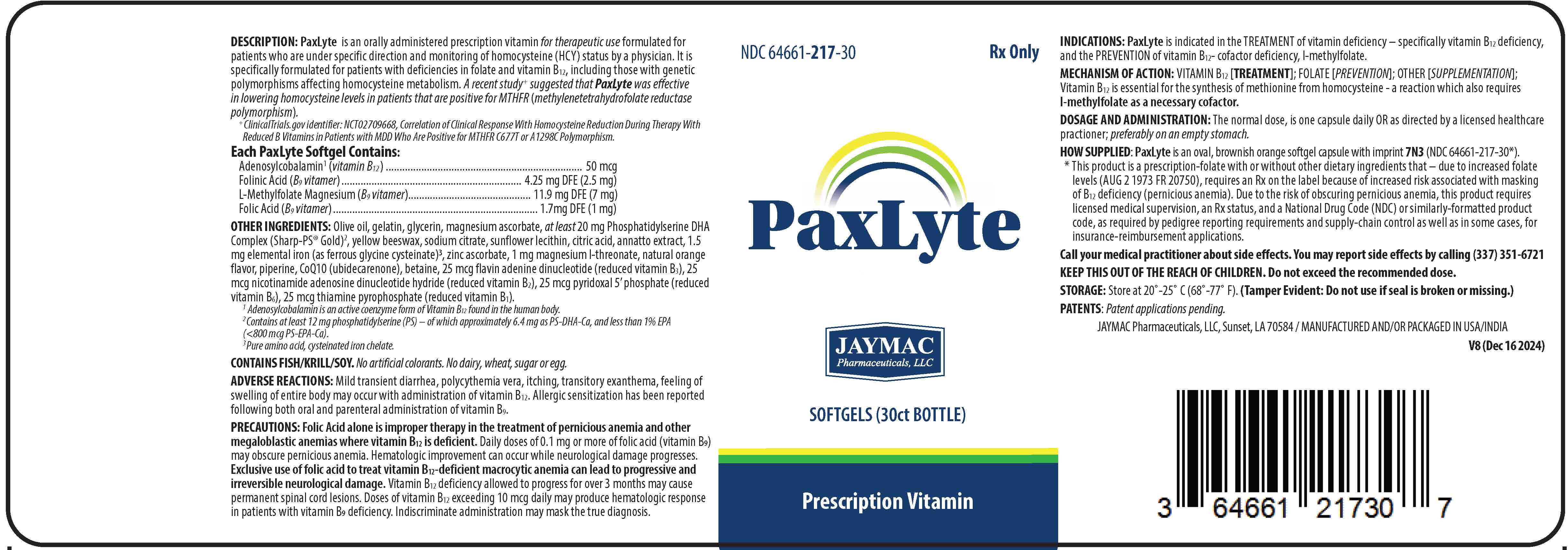 DRUG LABEL: PaxLyte
NDC: 64661-217 | Form: CAPSULE
Manufacturer: Jaymac Pharmaceuticals
Category: prescription | Type: HUMAN PRESCRIPTION DRUG LABEL
Date: 20251208

ACTIVE INGREDIENTS: LEUCOVORIN 2.5 mg/1 1; FOLIC ACID 1 mg/1 1; LEVOMEFOLATE MAGNESIUM 7 mg/1 1; FERROUS CYSTEINE GLYCINATE 13.6 mg/1 1; 1,2-DOCOSAHEXANOYL-SN-GLYCERO-3-PHOSPHOSERINE CALCIUM 6.4 mg/1 1; 1,2-ICOSAPENTOYL-SN-GLYCERO-3-PHOSPHOSERINE CALCIUM 800 ug/1 1; PHOSPHATIDYL SERINE 12 mg/1 1; PYRIDOXAL PHOSPHATE ANHYDROUS 25 ug/1 1; FLAVIN ADENINE DINUCLEOTIDE 025 ug/1 1; NADH 25 ug/1 1; COBAMAMIDE 50 ug/1 1; COCARBOXYLASE 25 ug/1 1; MAGNESIUM ASCORBATE 24 mg/1 1; ZINC ASCORBATE 1 mg/1 1; MAGNESIUM L-THREONATE 1 mg/1 1; BETAINE 500 mg/1 1; CITRIC ACID MONOHYDRATE 1.83 mg/1 1; SODIUM CITRATE 1.83 mg/1 1
INACTIVE INGREDIENTS: ANNATTO; GELATIN; GLYCERIN; LECITHIN, SUNFLOWER; OLIVE OIL; PIPERINE; WATER; UBIDECARENONE; YELLOW WAX

PaxLyte

DESCRIPTION

PaxLyte is an orally administered prescription vitamin for therapeutic use formulated for patients who are under specific direction and monitoring of homocysteine (HCY) status by a physician. It is specifically formulated for patients with deficiencies in folate and vitamin B12, including those with genetic polymorphisms affecting homocysteine metabolism. A recent study^+ suggested that PaxLyte was effective in lowering homocysteine levels in patients that are positive for MTHFR (methylenetetrahydrofolate reductase polymorphism).

^+ ClinicalTrials.gov identifier: NCT02709668, Correlation of Clinical Response With Homocysteine Reduction During Therapy With Reduced B Vitamins in Patients with MDD Who Are Positive for MTHFR C677T or A1298C Polymorphism.

CONTAINS

Each PaxLyte Softgel Contains:

Adenosylcobalamin^1 (vitamin B12) .......................... 50 mcg

Folinic Acid (B9 vitamer).......................................... 4.25 mg DFE (2.5 mg)

Folic Acid (B9 vitamer)............................................ 1.7 mg DFE (1 mg)

L-Methylfolate Magnesium (B9 vitamer)..................... 11.9 mg DFE (7 mg)

OTHER INGREDIENTS: Olive oil, gelatin, glycerin, magnesium ascorbate, at least 20 mg Phosphatidylserine DHA Complex (Sharp-PS® Gold)^2, yellow beeswax, sodium citrate, sunflower lecithin, citric acid, annatto extract, 1.5 mg elemental iron (as ferrous glycine cysteinate)^3, zinc ascorbate, 1 mg magnesium l-threonate, natural orange flavor, piperine, CoQ10 (ubidecarenone), betaine, 25 mcg flavin adenine dinucleotide (reduced vitamin B3), 25 mcg nicotinamide adenosine dinucleotide hydride (reduced vitamin B2), 25 mcg pyridoxal 5’ phosphate (reduced vitamin B6), 25 mcg thiamine pyrophosphate (reduced vitamin B1).

^1 Adenosylcobalamin is an active coenzyme form of Vitamin B12 found in the human body.

^2 Contains at least 12 mg phosphatidylserine (PS) – of which approximately 6.4 mg as PS-DHA-Ca, and less than 1% EPA (<800 mcg PS-EPA-Ca).

^3 Pure amino acid, cysteinated iron chelate. CONTAINS FISH/KRILL/SOY. No artificial colorants. No dairy, wheat, sugar or egg.

CONTAINS FISH/KRILL/SOY. No artificial colorants. No dairy, wheat, sugar or egg.

INDICATION

PaxLyte is indicated in the TREATMENT of vitamin deficiency – specifically vitamin B12 deficiency, and the PREVENTION of vitamin B12-cofactor deficiency, l-methylfolate.

MECHANISM OF ACTION

VITAMIN B12 [TREATMENT]; FOLATE [PREVENTION]; OTHER [SUPPLEMENTATION]; Vitamin B12 is essential for the synthesis of methionine from homocysteine - a reaction which also requires l-methylfolate as a necessary cofactor.

DOSAGE AND ADMINISTRATION

The normal dose, is one capsule daily OR as directed by a licensed healthcare practioner; preferably on an empty stomach.

HOW SUPPLIED

PaxLyte is an oval, brownish orange softgel capsule with imprint 7N3 (NDC 64661-217-30*).

* This product is a prescription-folate with or without other dietary ingredients that – due to increased folate levels (AUG 2 1973 FR 20750), requires an Rx on the label because of increased risk associated with masking of B12 deficiency (pernicious anemia). Due to the risk of obscuring pernicious anemia, this product requires licensed medical supervision, an Rx status, and a National Drug Code (NDC) or similarly-formatted product code, as required by pedigree reporting requirements and supply-chain control as well as in some cases, for insurance-reimbursement applications.

PRECAUTIONS

Folic Acid alone is improper therapy in the treatment of pernicious anemia and other megaloblastic anemias where vitamin B12 is deficient. Daily doses of 0.1 mg or more of folic acid (vitamin B9) may obscure pernicious anemia. Hematologic improvement can occur while neurological damage progresses. Exclusive use of folic acid to treat vitamin B12-deficient macrocytic anemia can lead to progressive and irreversible neurological damage. Vitamin B12 deficiency allowed to progress for over 3 months may cause permanent spinal cord lesions. Doses of vitamin B12 exceeding 10 mcg daily may produce hematologic response in patients with vitamin B9 deficiency. Indiscriminate administration may mask the true diagnosis.

ADVERSE REACTIONS

Mild transient diarrhea, polycythemia vera, itching, transitory exanthema, feeling of swelling of entire body may occur with administration of vitamin B12. Allergic sensitization has been reported following both oral and parenteral administration of vitamin B9.